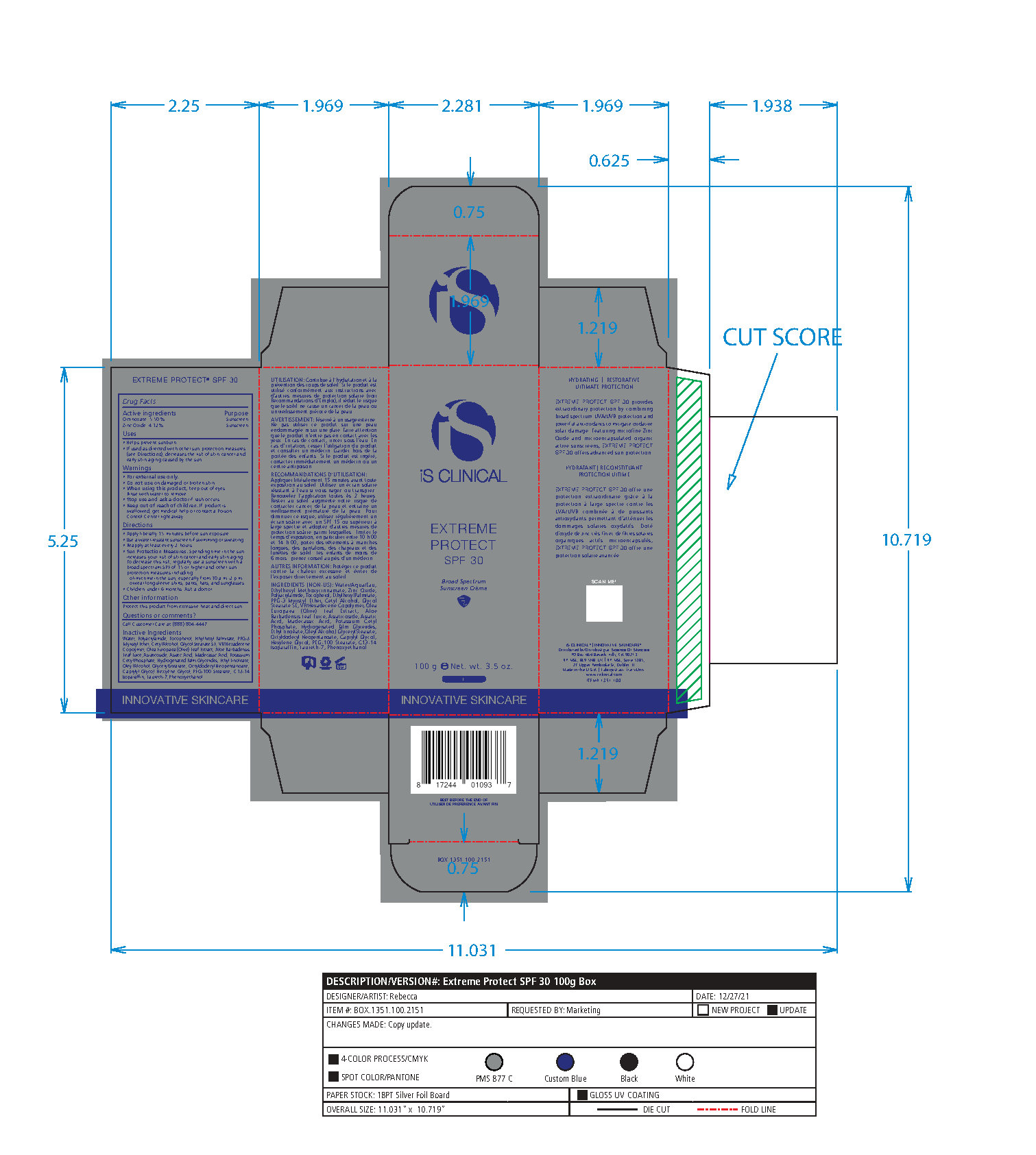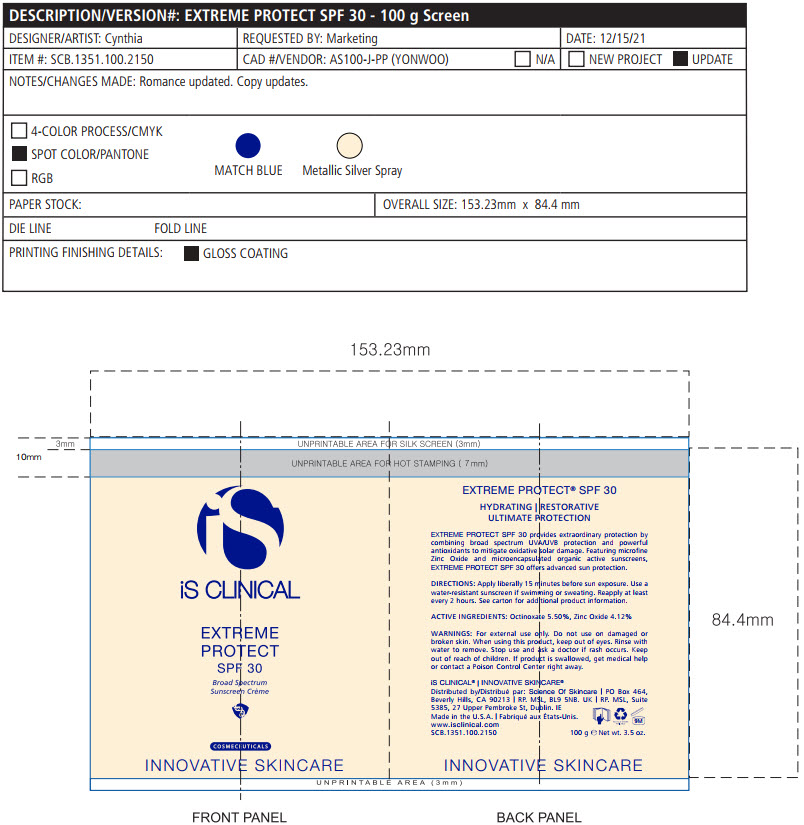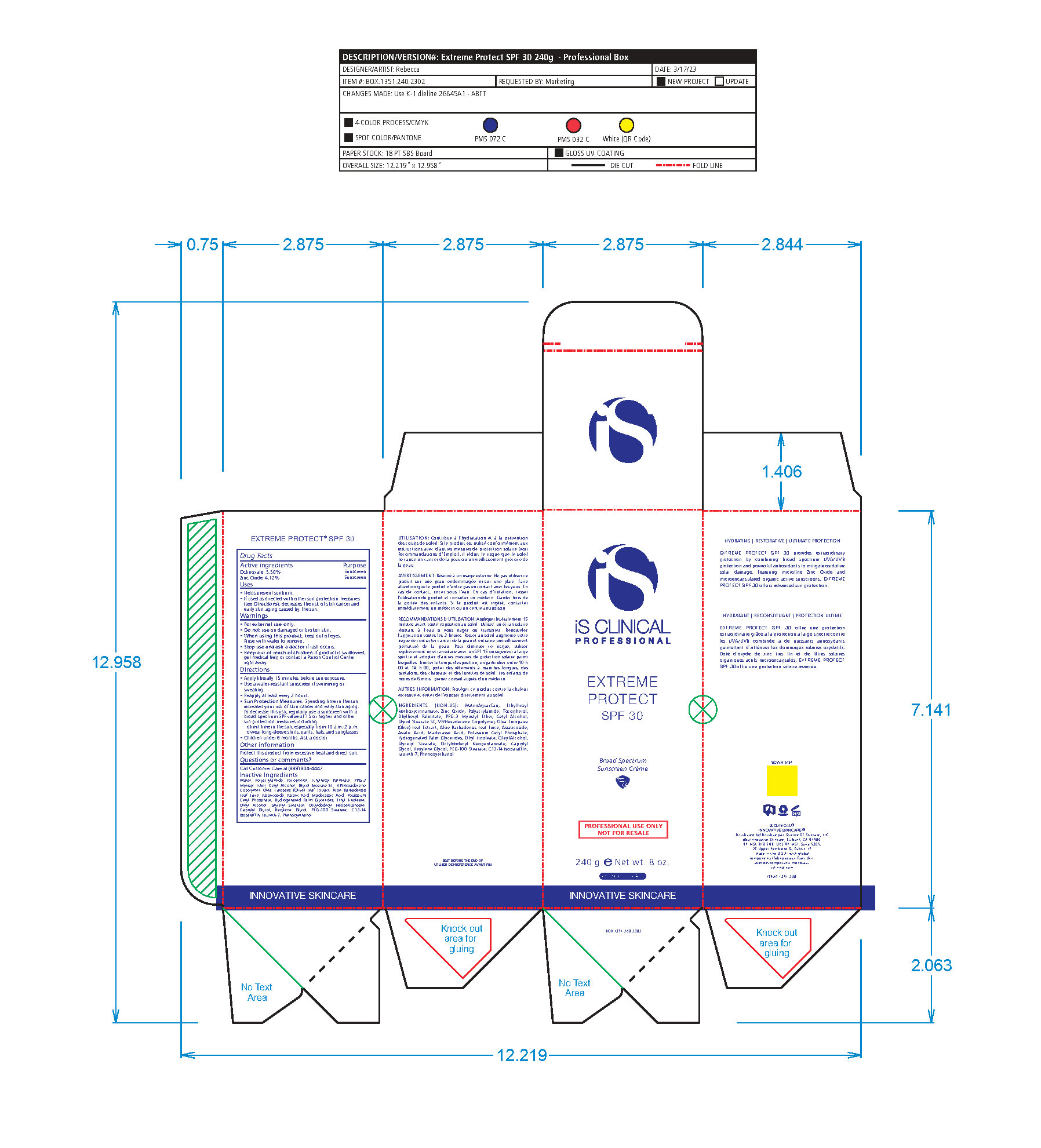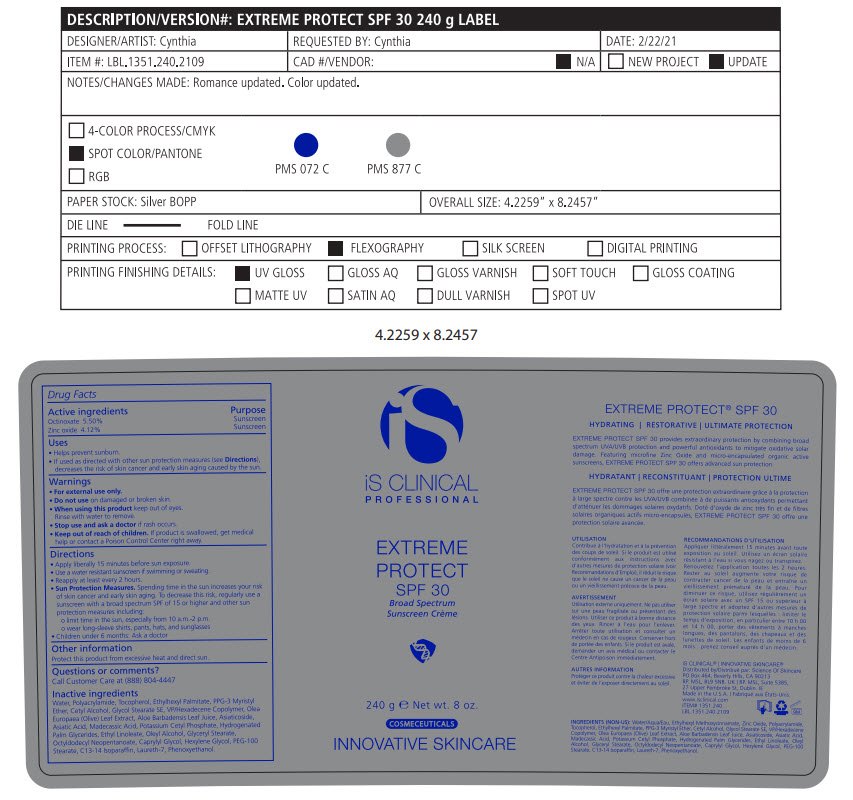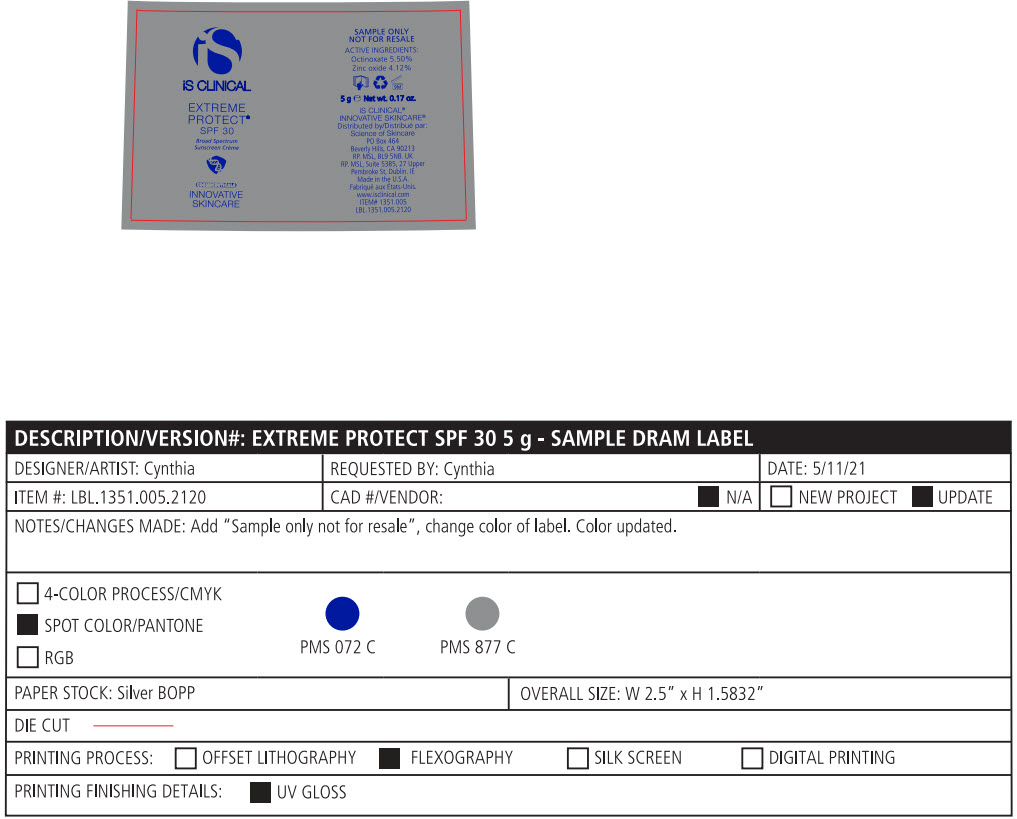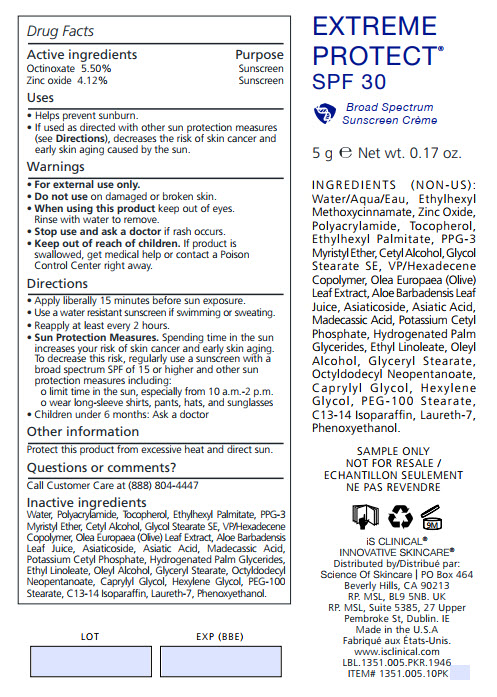 DRUG LABEL: EXTREME PROTECT SPF 30
NDC: 69219-103 | Form: LOTION
Manufacturer: SCIENCE OF SKINCARE LLC
Category: otc | Type: HUMAN OTC DRUG LABEL
Date: 20250109

ACTIVE INGREDIENTS: OCTINOXATE 5.5 g/100 g; ZINC OXIDE 4.12 g/100 g
INACTIVE INGREDIENTS: WATER; POLYACRYLAMIDE (1500 MW); TOCOPHEROL; ETHYLHEXYL PALMITATE; PPG-3 MYRISTYL ETHER; CETYL ALCOHOL; GLYCOL STEARATE SE; VINYLPYRROLIDONE/HEXADECENE COPOLYMER; OLEA EUROPAEA LEAF; ALOE VERA LEAF; ASIATICOSIDE; ASIATIC ACID; MADECASSIC ACID; SODIUM DIHYDROXYCETYL PHOSPHATE; ETHYL LINOLEATE; OLEYL ALCOHOL; GLYCERYL MONOSTEARATE; OCTYLDODECYL NEOPENTANOATE; CAPRYLYL GLYCOL; HEXYLENE GLYCOL; PEG-100 STEARATE; C13-14 ISOPARAFFIN; LAURETH-7; PHENOXYETHANOL

Extreme Protect SPF 30

Active Ingredients

Octinoxate – 5.50%

Zinc Oxide – 4.12%

PURPOSE

SUNSCREEN

USES

• Helps prevent sunburn.
• If used as directed with other sun protection measures (see Directions), decreases the risk of skin cancer and early skin aging caused by the sun

WARNINGS

• For external use only

• Do not use on damaged or broken skin

• When using this product keep out of eyes. Rinse with water to remove.

• Stop use and ask a doctor if rash occurs

- Keep out of reach of children. If product is swallowed,get medical help or contact a Poison Control Center right away.

DIRECTIONS

- APPLY LIBERALLY 15 MINUTES BEFORE SUN EXPOSURE.

• Use a water resistant sunscreen if swimming or sweating

• Reapply at least every 2 hours

• Sun Protection Measures. Spending time in the sun increases your risk of skin cancer and early skin aging. To decrease this risk, regularly use a sunscreen with a broad spectrum SPF of 15 or higher and other sun protection measures including:
o limit time in the sun, especially from 10 a.m.-2 p.m.
o wear long-sleeve shirts, pants, hats, and sunglasses
• Children under 6 months: Ask a doctor

Other Information

PROTECT THIS PRODUCT FROM EXCESSIVE HEAT AND DIRECT SUN.

Questions or Comments?

Call Customer Care at (888) 804-4447

Inactive Ingredients

Water, Polyacrylamide, Tocopherol, Ethylhexyl Palmitate, PPG-3 Myristyl Ether, Cetyl Alcohol, Glycol Stearate SE, VP/Hexadecene Copolymer, Olea Europaea (Olive) Leaf Extract, Aloe Barbadensis Leaf Juice, Asiaticoside, Asiatic Acd, Madecassic Acid, Sodium Dihydrocetyl Phosphate, Ethyl Linoleate, Oleyl Alcohol, Glyceryl Stearate, Octyldodecyl Neopentanoate, Caprylyl Glycol, Hexylene Glycol, PEG-100 Stearate, C13-14 Isoparaffin, Laureth-7, Phenoxyethanol.